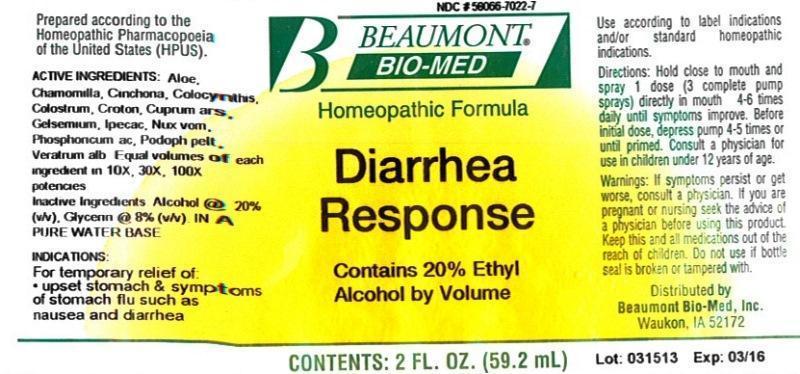 DRUG LABEL: Diarrhea Response
NDC: 58066-7022 | Form: LIQUID
Manufacturer: Beaumont Bio Med
Category: homeopathic | Type: HUMAN OTC DRUG LABEL
Date: 20150109

ACTIVE INGREDIENTS: ALOE 10 [hp_X]/59.2 mL; MATRICARIA RECUTITA 10 [hp_X]/59.2 mL; CINCHONA OFFICINALIS BARK 10 [hp_X]/59.2 mL; CITRULLUS COLOCYNTHIS FRUIT PULP 10 [hp_X]/59.2 mL; BOS TAURUS COLOSTRUM 10 [hp_X]/59.2 mL; CROTON TIGLIUM SEED 10 [hp_X]/59.2 mL; CUPRIC ARSENITE 10 [hp_X]/59.2 mL; GELSEMIUM SEMPERVIRENS ROOT 10 [hp_X]/59.2 mL; IPECAC 10 [hp_X]/59.2 mL; STRYCHNOS NUX-VOMICA SEED 10 [hp_X]/59.2 mL; PHOSPHORIC ACID 10 [hp_X]/59.2 mL; PODOPHYLLUM 10 [hp_X]/59.2 mL; VERATRUM ALBUM ROOT 10 [hp_X]/59.2 mL
INACTIVE INGREDIENTS: ALCOHOL; GLYCERIN; WATER

Diarrhea Response

ACTIVE INGREDIENT

HPUS active ingredients: Aloe socotrina, Chamomilla, Cinchona officinalis, Colocynthis, Colostrum, Croton tiglium, Cuprum arsenicosum, Gelsemium sempervirens, Ipecacuanha, Nux vomica, Phosphoricum acidum, Podophyllum peltatum, Veratrum album. Equal volumes of each ingredient in 10X, 30X, 100X potencies.

INACTIVE INGREDIENT

Inactive Ingredients: Alcohol @ 20% (v/v), Glycerin @ 8% (v/v), in a pure water base

INDICATIONS AND USAGE

Indications: For temporary relief of: upset stomach and symptoms of stomach flu such as nausea and diarrhea.

Use according to label indications and/or standard homeopathic indications.

DOSAGE AND ADMINISTRATION

Directions: Hold close to mouth and spray 1 dose (3 complete pump sprays) directly in mouth 4-6 times daily until symptoms improve. Before initial dose, depress pump 4-5 times or until primed. Consult a physician for use in children under 12 years of age.

WARNINGS

Warnings: If symptoms persist or get worse, consult a physician. If you are pregnant or nursing seek the advice of a physician before using this product. Keep this and all medications out of the reach of children. Do not use if bottle seal is broken or tampered with.

- Keep out of reach of children.

PURPOSE

For temporary relief of:

- upset stomach and symptoms of stomach flu such as nausea and diarrhea.

Use according to label indications and/or standard homeopathic indications.